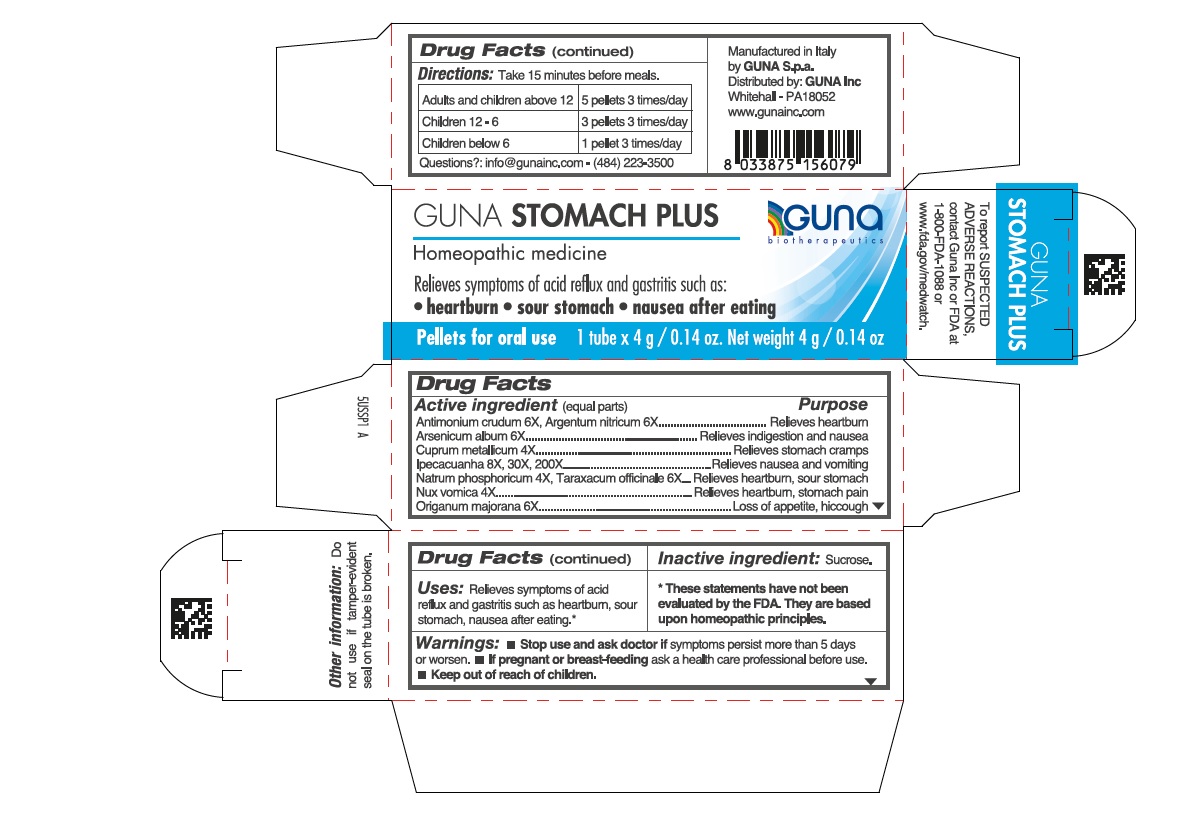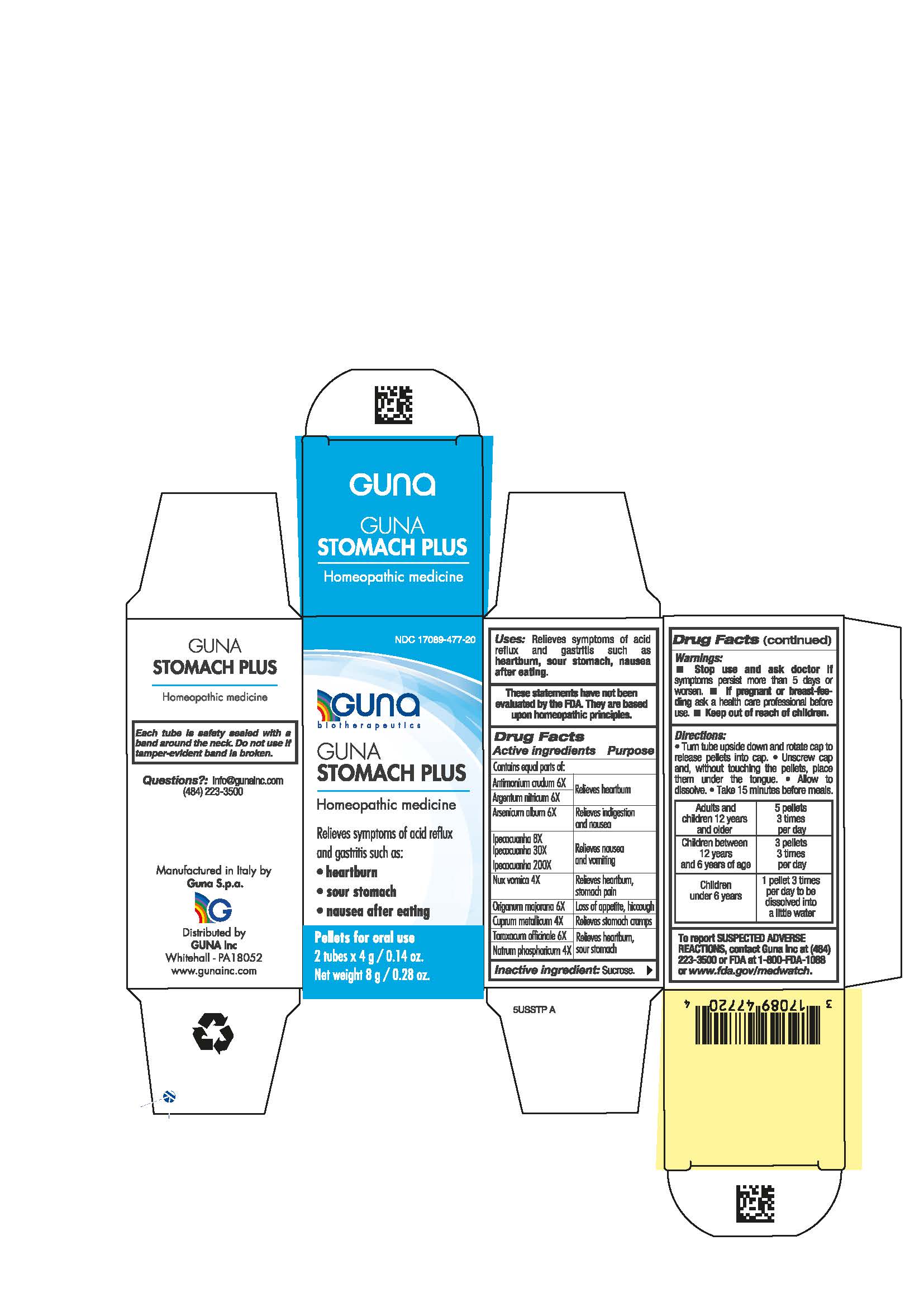 DRUG LABEL: GUNA STOMACH PLUS
NDC: 17089-477 | Form: PELLET
Manufacturer: Guna spa
Category: homeopathic | Type: HUMAN OTC DRUG LABEL
Date: 20211215

ACTIVE INGREDIENTS: STRYCHNOS NUX-VOMICA SEED 4 [hp_X]/4 g; ANTIMONY TRISULFIDE 6 [hp_X]/4 g; COPPER 4 [hp_X]/4 g; IPECAC 8 [hp_X]/4 g; SILVER NITRATE 6 [hp_X]/4 g; ORIGANUM MAJORANA 6 [hp_X]/4 g; TARAXACUM OFFICINALE ROOT 6 [hp_X]/4 g; SODIUM PHOSPHATE, DIBASIC, HEPTAHYDRATE 4 [hp_X]/4 g; ARSENIC TRIOXIDE 6 [hp_X]/4 g
INACTIVE INGREDIENTS: SUCROSE 4 g/4 g

GUNA STOMACH PLUS

ACTIVE INGREDIENTS/PURPOSE

Antimonium crudum 6X Relieves heartburn

Argentum nitricum 6X Relieves heartburn

Arsenicum album 6X Relieves indigestion and nausea

Ipecacuanha 8X, 30X, 200X Relieves nausea and vomiting

Nux vomica 4X Relieves heartburn, stomach pain

Origanum majorana 6X Loss of appetite, hiccough

Cuprum metallicum 4X Relieves stomach cramps

Taraxacum officinale 6X Relieves heartburn, sour stomach

Natrum phosphoricum 4X Relieves heartburn, sour stomach

- Stop use and ask doctor if symptoms persist more than 5 days or worsen.
- If pregnant or breast-feeding ask a health professional before use.
- Keep out of reach of children.

USES

Relieves symptoms of acid reflux and gastritis such as:

- heartburn
- sour stomach
- nausea after eating

INDICATIONS AND USAGE

Relieves symptoms of acid reflux and gastritis such as:

- heartburn
- sour stomach
- nausea after eating

QUESTIONS

info@gunainc.com
(484) 223-3500

WARNINGS

Keep out of reach of children

PREGNANCY

If pregnant or breast-feeding ask a health care professional before use.

WARNINGS

- Stop use and ask doctor if symptoms persist more than 5 days or worsen.
- If pregnant or breast-feeding ask a health care professional before use
- keep out of reach of children

DIRECTIONS

- Turn tube upside down and rotate cap to release pellets into cap. ● Unscrew cap and, without touching the pellets, place them under the tongue. ● Allow to dissolve. ● Take 15 minutes before meals.

DOSAGE AND ADMINISTRATION

- Adults and children 12 years and older 5 pellets 3 times per day
- Children between 12 and 6 years of age 3 pellets 3 times per day
- Children under 6 years 1 pellet 3 times per day to be disoolved into a little water

Inactive ingredient: Sucrose.

- Keep out of reach of children